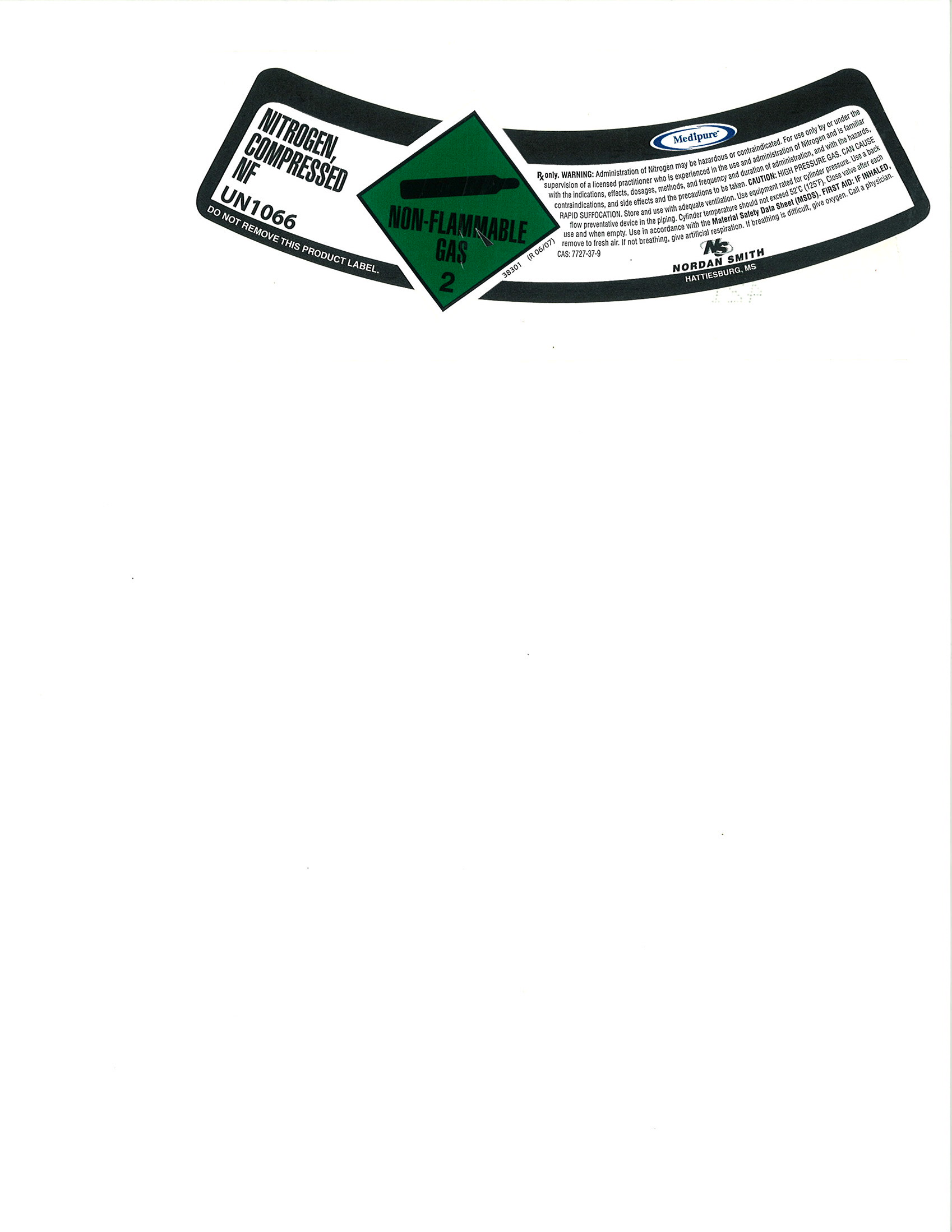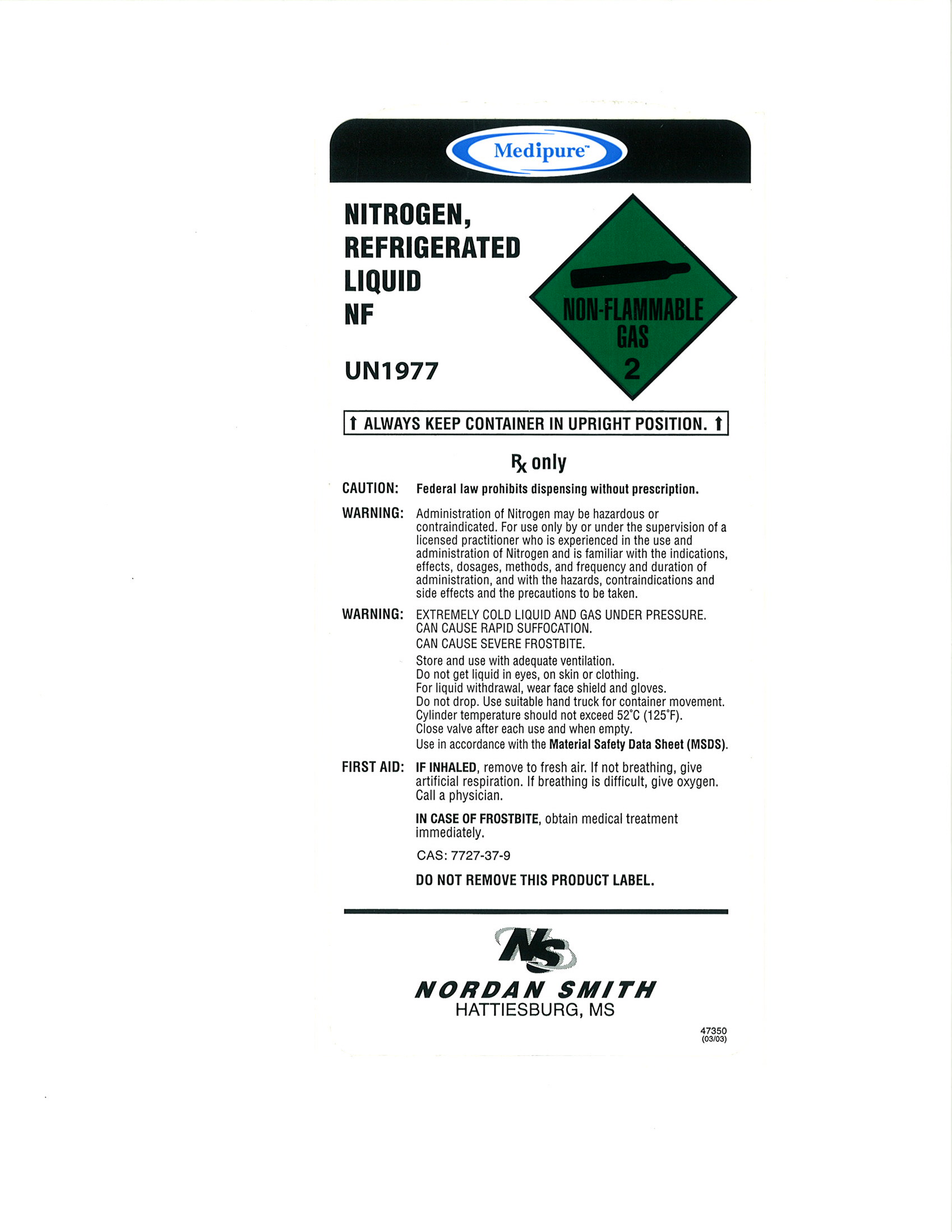 DRUG LABEL: Nitrogen
NDC: 54416-002 | Form: GAS
Manufacturer: Nordan Smith Welding Supply
Category: prescription | Type: HUMAN PRESCRIPTION DRUG LABEL
Date: 20100909

ACTIVE INGREDIENTS: Nitrogen 995 mL/1 L

Nitrogen

PACKAGE LABEL

NITROGEN, COMPRESSED NF
UN1066
DO NOT REMOVE THIS PRODUCT LABEL.
NON-FLAMMBLE GAS 2
Medipure
RX only. WARNING: Administration of Nitrogen may be hazardous or contraindicated. For use only by or under the supervision of a licensed practitioner who is experienced in the use and administration of Nitrogen and is familiar with the indications, effects, dosages, methods, and frequency and duration of administration, and with the hazards, contraindications, and side effects and the precautions to be taken. CAUTION: HIGH PRESSURE GAS. CAN CAUSE RAPID SUFFOCATION. Store and use with adequate ventilation. Use equipment rated for cylinder pressure. Use a back flow preventative device in the piping. Cylinder temperature should not exceed 52° (125°). Close valve after each use and when empty. Use in accordance with the Material Safety Data Sheet (MSDS). FIRST AID: IF INHALED, remove to fresh air. If not breathing, give artificial respiration. If breathing is difficult, give oxygen. Call a physician. CAS:7727-37-9
N/S NORDAN SMITH HATTIESBURG, MS. 38301 (R 06/07)

PACKAGE LABEL

Medipure
NITROGEN, REFRIGERATED LIQUID NF
UN1977
NON-FLAMMABLE GAS 2
ALWAYS KEEP CONTAINER IN UPRIGHT POSITION.
RX ONLY
CAUTION: Federal law prohibits dispensing without prescription.
WARNING: Administration of Nitrogen may be hazardous or contraindicated. For use only by or under the supervision of a licensed practitioner who is experienced in the use and administration of Nitrogen and is familiar with the indications, administration of Nitrogen and is with the indications, effects, dosages, methods, and frequency and duration of administration and with the hazards, contraindications and side effects and the precautions to be taken.
WARNING: EXTREMELY COLD LIQUID AND GAS UNDER PRESSURE, CAN CAUSE RAPID SUFFOCATION. CAN CAUSE SEVERE FROSTBITE. Store and use with adequate ventilation. Do not get liquid in eyes, on skin or clothing. For liquid withdrawal, wear face shield and gloves. Do not drop. Use suitable hand truck for container movement. Cylinder temperature should not exceed 52°C (125°F). Close valve after each use and when empty. Use in accordance with the Material Safety Data Sheet (MSDS).
FIRST AID: IF INHALED, remove to fresh air. If not breathing, give artificial respiration. If breathing is difficult, give oxygen. Call a physician. IN CASE OF FROSTBITE, obtain medical treatment immediately.
CAS: 7727-37-9
DO NOT REMOVE THIS PRODUCT LABEL.
N/S NORDAN SMITH HATTIESBURG, MS.
47350 (03/03)